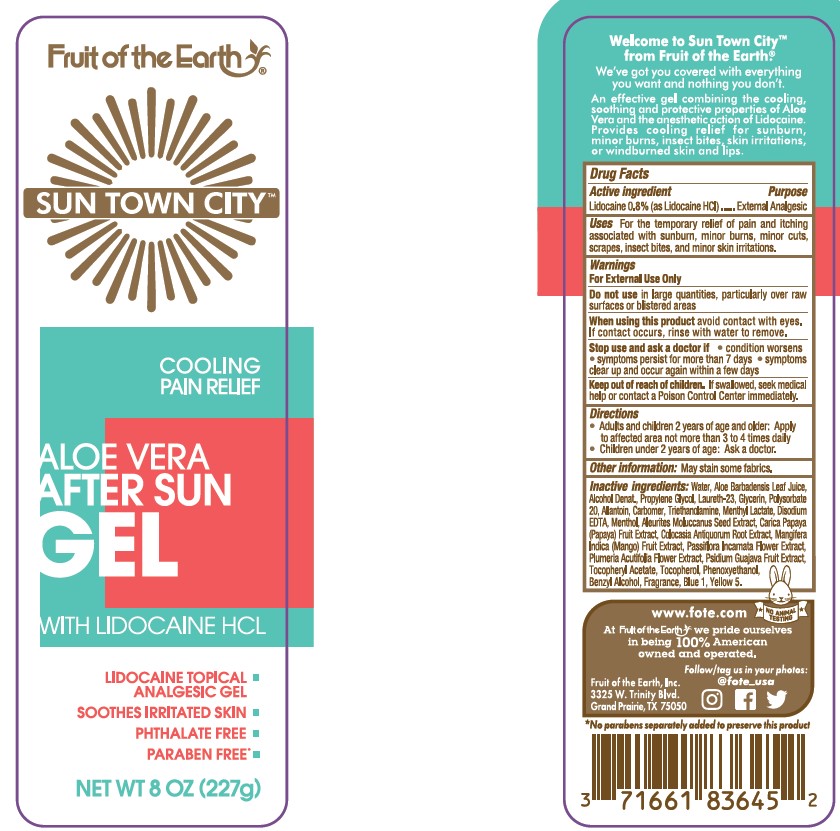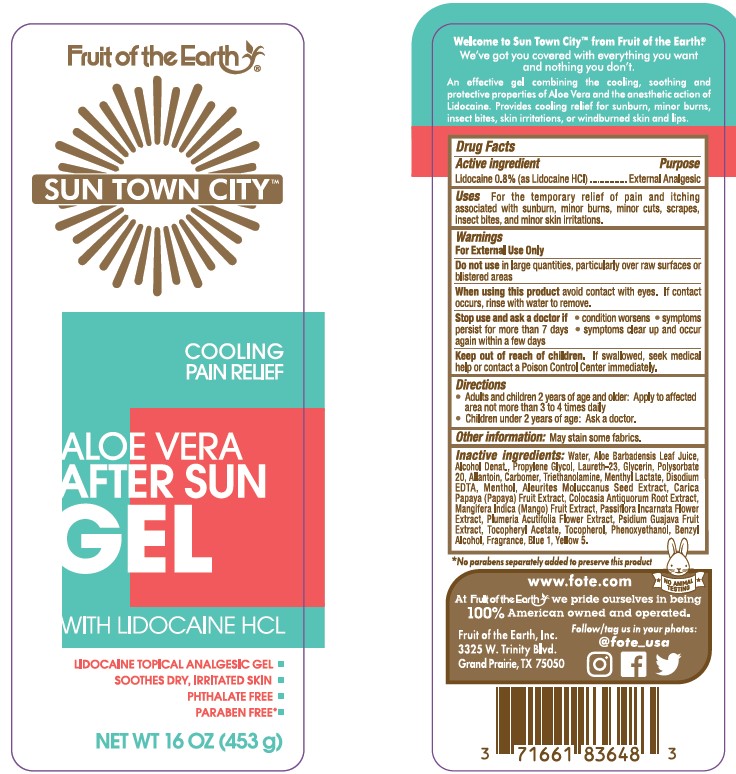 DRUG LABEL: Fruit of the Earth Sun Town City Aloe Vera After Sun with Lidocaine HCL
NDC: 62217-070 | Form: GEL
Manufacturer: Fruit of the Earth, Inc.
Category: otc | Type: HUMAN OTC DRUG LABEL
Date: 20241017

ACTIVE INGREDIENTS: LIDOCAINE 8 mg/1 g
INACTIVE INGREDIENTS: WATER; ALOE VERA LEAF; ALCOHOL; PROPYLENE GLYCOL; LAURETH-23; POLYSORBATE 20; GLYCERIN; ALLANTOIN; .ALPHA.-TOCOPHEROL ACETATE; PHENOXYETHANOL; CARBOMER INTERPOLYMER TYPE A (55000 CPS); TROLAMINE; MENTHYL LACTATE, (-)-; BENZYL ALCOHOL; EDETATE DISODIUM; MENTHOL; .ALPHA.-TOCOPHEROL, DL-; PLUMERIA RUBRA FLOWER; MANGO; GUAVA; PAPAYA; PASSIFLORA INCARNATA FLOWER; COLOCASIA ESCULENTA ROOT; ALEURITES MOLUCCANA SEED; FD&C BLUE NO. 1; FD&C YELLOW NO. 5

Fruit of the Earth Sun Town City Aloe Vera After Sun Gel with Lidocaine HCL

Active Ingredients

Lidocaine 0.8% (as Lidocaine HCl)

Purpose

External Analgesic

Uses

For the temporary relief of pain and itching associated with sunburn, minor burns, minor cuts, scrapes, insect bites, and minor skin irritations.

Warnings

For External Use Only

Do not use

in large quantities, particularly over raw surfaces or blistered areas

When using this product

avoid contact with eyes. If contact occurs, rinse with water to remove.

Stop use and ask a doctor if

• condition worsens • symptoms persist for more than 7 days • symptoms clear up and occur again within a few days

Keep out of reach of children.

If swallowed, seek medical help or contact a Poison Control Center immediately.

Directions

- Adults and children 2 years of age and older: Apply to affected area not more than 3 to 4 times daily
- Children under 2 years of age: Ask a doctor.

Other information:

May stain some fabrics.

Inactive ingredients:

water, aloe barbadensis leaf juice, alcohol denat., propylene glycol, laureth-23, glycerin, polysorbate 20, allantoin, carbomer, triethanolamine, menthyl lactate, disodium EDTA, menthol, aleurites moluccarnus seed extract, carica papaya (papaya) fruit extract, colocasia antiquorum root extract, mangifera indica (mango) fruit extract, passiflora incarnata flower extract, plumeria acutifolia flower extract, psidium guajava fruit extract, tocopheryl acetate, tocopherol, phenoxyethanol, benzyl alcohol, fragrance, Blue 1, Yellow 5.